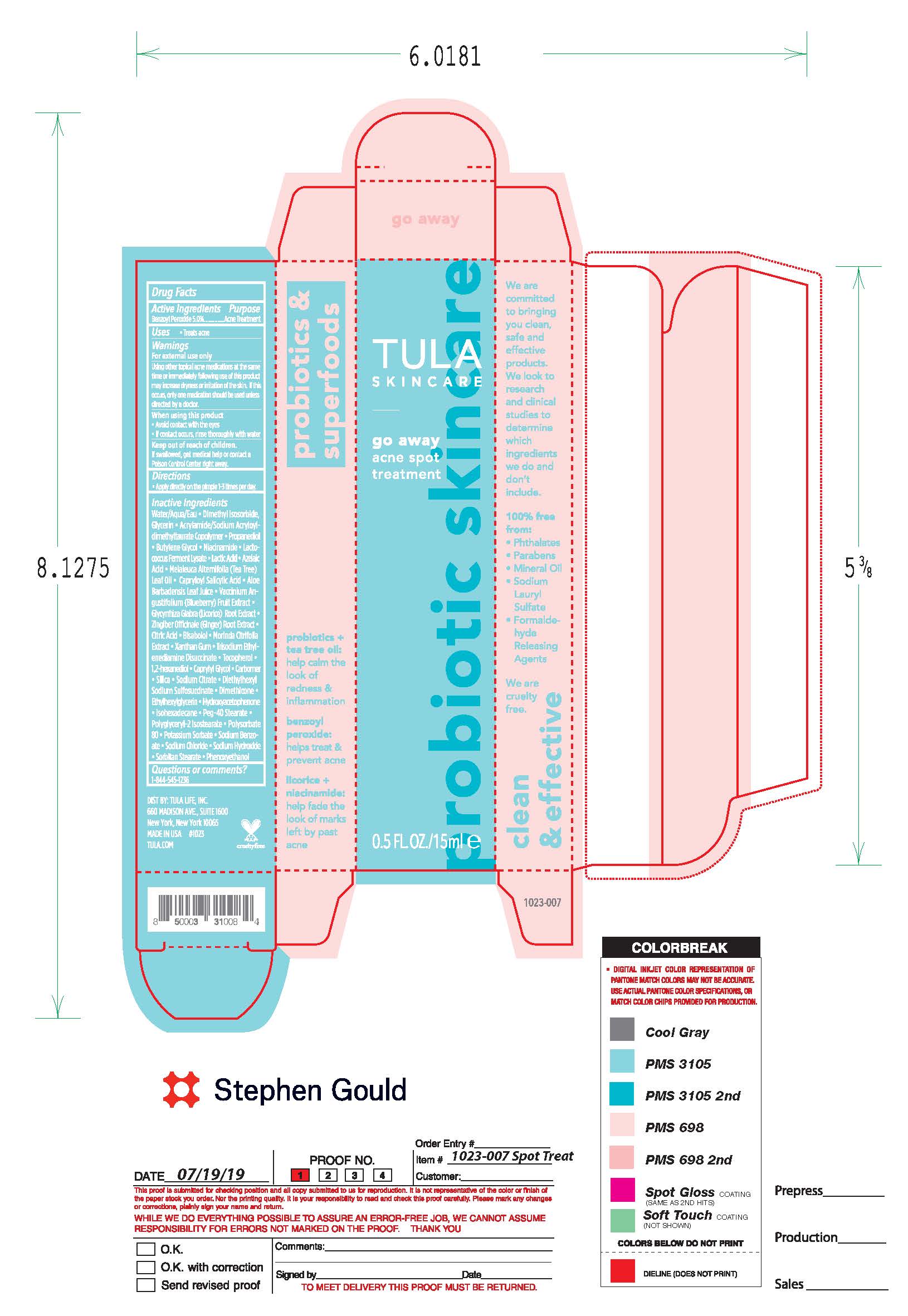 DRUG LABEL: TULA Skincare Go Away Acne Spot Treatment
NDC: 72296-040 | Form: LIQUID
Manufacturer: Tula Life LLC
Category: otc | Type: HUMAN OTC DRUG LABEL
Date: 20221231

ACTIVE INGREDIENTS: BENZOYL PEROXIDE 5 g/100 g
INACTIVE INGREDIENTS: WATER; DIMETHYL ISOSORBIDE; GLYCERIN; PROPANEDIOL; BUTYLENE GLYCOL; NIACINAMIDE; LACTOCOCCUS LACTIS; LACTIC ACID; AZELAIC ACID; MELALEUCA ALTERNIFOLIA LEAF; CAPRYLOYL SALICYLIC ACID; ALOE VERA LEAF; VACCINIUM ANGUSTIFOLIUM LEAF; GLYCYRRHIZA GLABRA; ZINGIBER OFFICINALE WHOLE; CITRIC ACID ACETATE; .ALPHA.-BISABOLOL, (+)-; MORINDA CITRIFOLIA FRUIT; PHENOXYETHANOL; XANTHAN GUM; SODIUM CHLORIDE; SODIUM HYDROXIDE; SODIUM BENZOATE; SORBITAN OLIVATE; TRISODIUM ETHYLENEDIAMINE DISUCCINATE; ETHYLHEXYLGLYCERIN; TOCOPHEROL; 1,2-HEXANEDIOL; CARBOMER 940; SODIUM CITRATE; DIMETHICONE; HYDROXYACETOPHENONE; ISOHEXADECANE; PEG-40 STEARATE; POLYGLYCERYL-2 ISOSTEARATE; POLYSORBATE 80; BLUEBERRY

DRUG FACTS

Active Ingredients

Benzoyl Peroxide 5.0%

Purpose

Acne Treatment

Uses

• treats acne

• Helps prevent the development or new acne blemishes

Warnings

For external use only
Using other topical medications at the same time or
immediately following use of this product may increase
dryness or irritation of the skin. If this occurs, only one
medication should be used unless directed by a doctor.

When using this product
• avoid contact with the eyes
• if contact occurs, rinse thoroughly with water

Keep out of reach of children. If swallowed, get medical help
or contact a Poison Control Center right away.

Directions

• clean the skin thoroughly before applying this product
• cover the entire affected area with a thin layer one to three
times daily
• because excessive drying of the skin may occur, start with
one application daily, then gradually increase to two or three
times daily if needed or as directed by a doctor
• if bothersome dryness or peeling occurs, reduce application
to once a day or every other day

Inactive ingredients

Aqua/Water/Eau, Dimethyl Isosorbide, Glycerin, Acrylamide/Sodium Acryloyldimethyltaurate Copolymer, Propanediol, Butylene Glycol, Niacinamide, Lactococcus Ferment Lysate, Lactic Acid, Azelaic Acid, Melaleuca Alternifolia (Tea Tree) Leaf Oil, Capryloyl Salicylic Acid, Aloe Barbadensis Leaf Juice, Vaccinium Angustifolium (Blueberry) Fruit Extract, Glycyrrhiza Glabra (Licorice) Root Extract, Zingiber Officinale (Ginger) Root Extract, Citric Acid, Bisabolol, Morinda Citrifolia Extract, Xanthan Gum, Trisodium Ethylenediamine Disuccinate, Tocopherol, 1,2-Hexanediol, Caprylyl Glycol, Carbomer, Silica, Sodium Citrate, Diethylhexyl Sodium Sulfosuccinate, Dimethicone, Ethylhexylglycerin, Hydroxyacetophenone, Isohexadecane, PEG-40 Stearate, Polyglyceryl-2 Isostearate, Polysorbate 80, Potassium Sorbate, Sodium Benzoate, Sodium Chloride, Sodium Hydroxide, Sorbitan Stearate, Phenoxyethanol

Questions or Comments?

1-844-545-1236